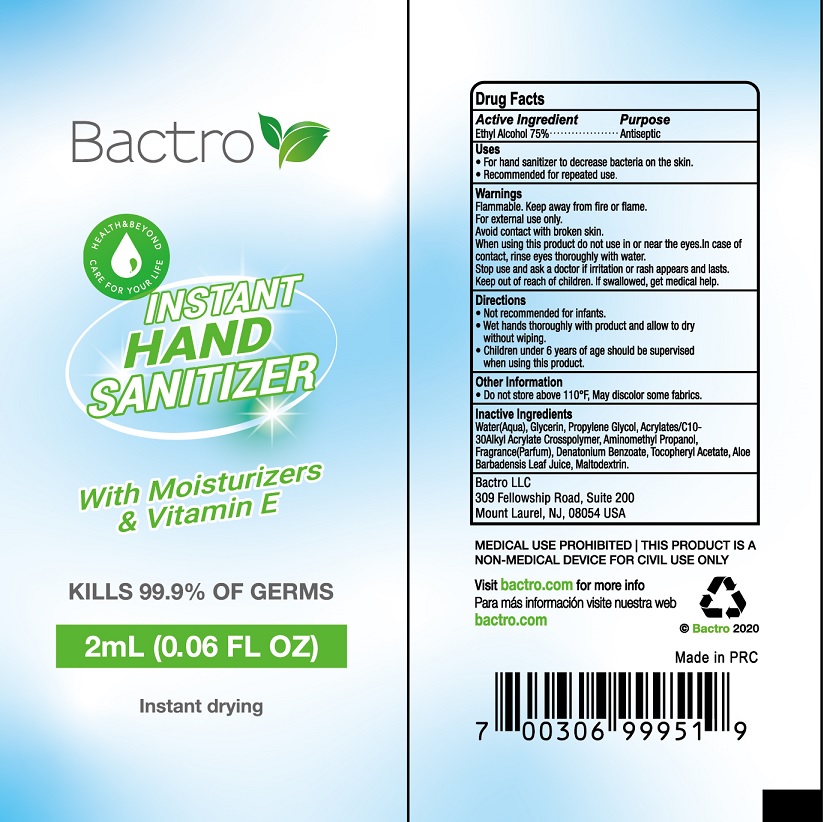 DRUG LABEL: Bactro Instant hand sanitizer
NDC: 71734-311 | Form: LIQUID
Manufacturer: JIANGMEN SHUIZIRUN SANITARY ARTICLES CO., LTD.
Category: otc | Type: HUMAN OTC DRUG LABEL
Date: 20200710

ACTIVE INGREDIENTS: ALCOHOL 75 mL/100 mL
INACTIVE INGREDIENTS: GLYCERIN; Propylene Glycol; WATER; TROLAMINE; EDETATE DISODIUM; CARBOMER COPOLYMER TYPE A; AMINOMETHYLPROPANOL; .ALPHA.-TOCOPHEROL ACETATE, D-; Denatonium Benzoate

Drug Fact

Active Ingredient

Ethyl Alcohol 75%

Purpose

Antiseptic

Uses

- Apply topically as needed to cleanse

Warnings

For external use only.

Flammable, keep from fire or flame.

Avoid contact with broken skin.

When using this product do not use in or near the eyes. In case of contact, rinse eyes thoroughly with water.

Stop use and ask a doctor if irritation or rah appears and lasts.

Other information

- Do not store above 110℉
- May discolor some fabrics.

Keep out of reach of children.

If swallowed, get medical help.

Directions

- Wet hands thoroughly with product and allow to dry without wiping.
- Children under 6 years of age should be supervised when using this product.
- Not recomended for infants.

Inactive Ingredients

Water (Aqua), Glycerin, Propylene Glycol, Acrylates/C10-30Alkyl Acrylate Crosspolymer, Ainomethyl Propanol, Fragrance (Parfum), Denatonium Benzoate, Tocopheryl Actate, Aloe Barbadensis Leaf Juice, Maltodextrin.